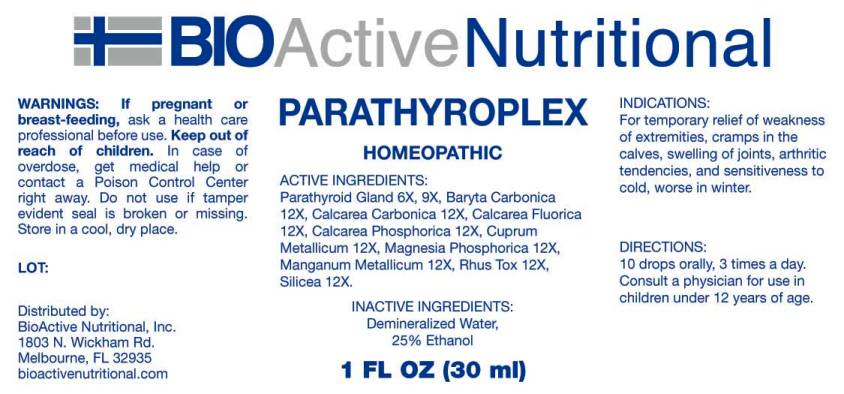 DRUG LABEL: Parathyroplex
NDC: 43857-0205 | Form: LIQUID
Manufacturer: BioActive Nutritional, Inc.
Category: homeopathic | Type: HUMAN OTC DRUG LABEL
Date: 20170418

ACTIVE INGREDIENTS: BOS TAURUS PARATHYROID GLAND 6 [hp_X]/1 mL; BARIUM CARBONATE 12 [hp_X]/1 mL; OYSTER SHELL CALCIUM CARBONATE, CRUDE 12 [hp_X]/1 mL; TRIBASIC CALCIUM PHOSPHATE 12 [hp_X]/1 mL; CALCIUM FLUORIDE 12 [hp_X]/1 mL; COPPER 12 [hp_X]/1 mL; MAGNESIUM PHOSPHATE, DIBASIC TRIHYDRATE 12 [hp_X]/1 mL; MANGANESE 12 [hp_X]/1 mL; TOXICODENDRON PUBESCENS LEAF 12 [hp_X]/1 mL; SILICON DIOXIDE 12 [hp_X]/1 mL
INACTIVE INGREDIENTS: WATER; ALCOHOL

Drug Facts:

ACTIVE INGREDIENTS:

Parathyroid Gland (Bovine) 6X, 9X, Baryta Carbonica 12X, Calcarea Carbonica 12X, Calcarea Fluorica 12X, Calcarea Phosphorica 12X, Cuprum Metallicum 12X, Magnesia Phosphorica 12X, Manganum Metallicum 12X, Rhus Tox 12X, Silicea 12X.

INDICATIONS:

For temporary relief of weakness of extremities, cramps in the calves, swelling of joints, arthritic tendencies, and sensitiveness to cold, worse in winter.

WARNINGS:

If pregnant or breast-feeding, ask a health care professional before use.

Keep out of reach of children. In case of overdose, get medical help or contact a Poison Control Center right away.

Do not use if tamper evident seal is broken or missing.

Store in a cool, dry place.

DIRECTIONS:

10 drops orally, 3 times a day. Consult a physician for use in children under 12 years of age.

INACTIVE INGREDIENTS:

Demineralized Water, 25% Ethanol

Keep out of reach of children. In case of overdose, get medical help or contact a Poison Control Center right away.

INDICATIONS:

For temporary relief of weakness of extremities, cramps in the calves, swelling of joints, arthritic tendencies, and sensitiveness to cold, worse in winter.

QUESTIONS:

Distributed by:

BioActive Nutritional, Inc.

1803 N. Wickham Rd.

Melbourne, FL 32935

bioactivenutritional.com

PACKAGE LABEL DISPLAY:

BIOActive Nutritional

PARATHYROPLEX

HOMEOPATHIC

1 FL OZ (30 ml)